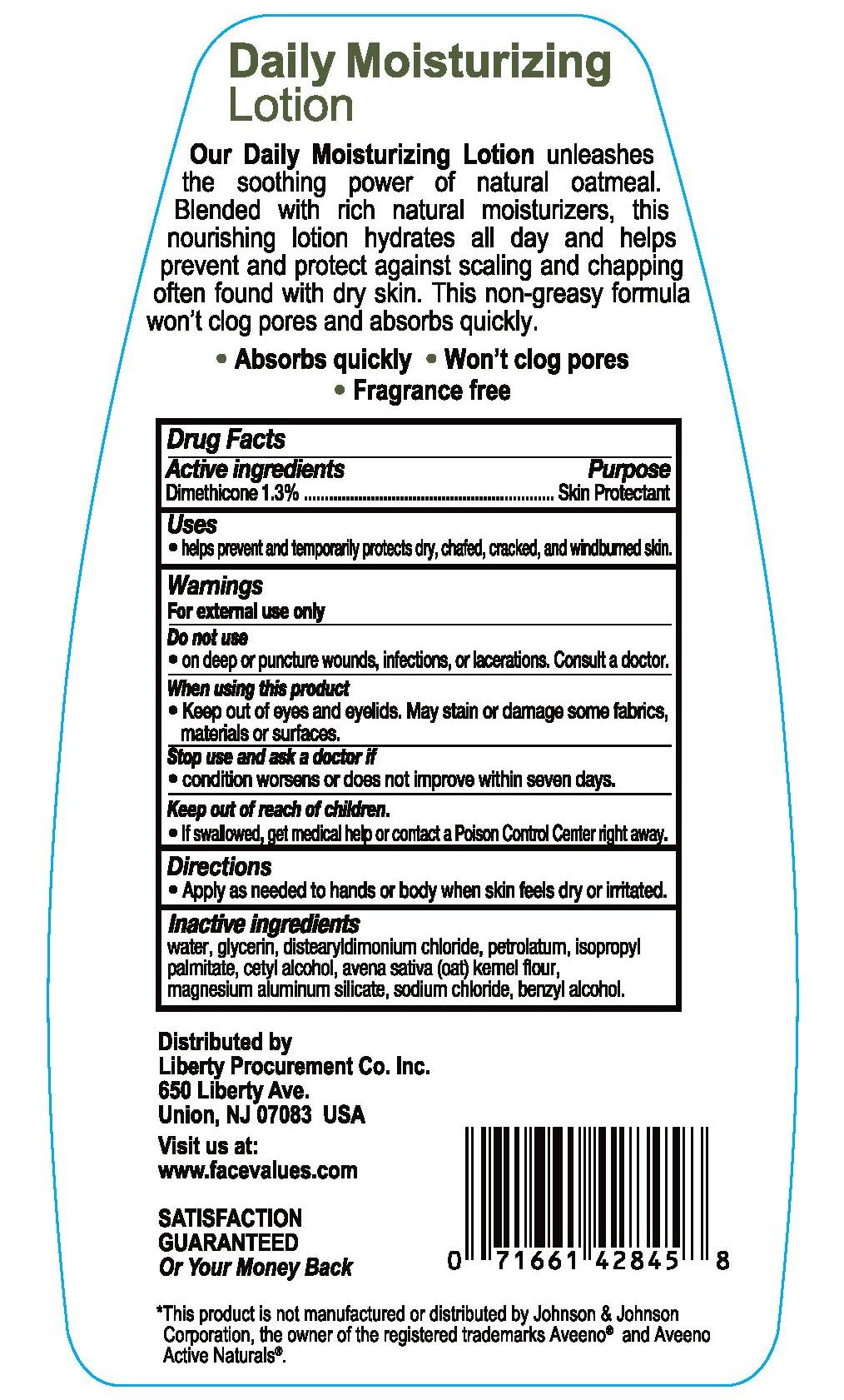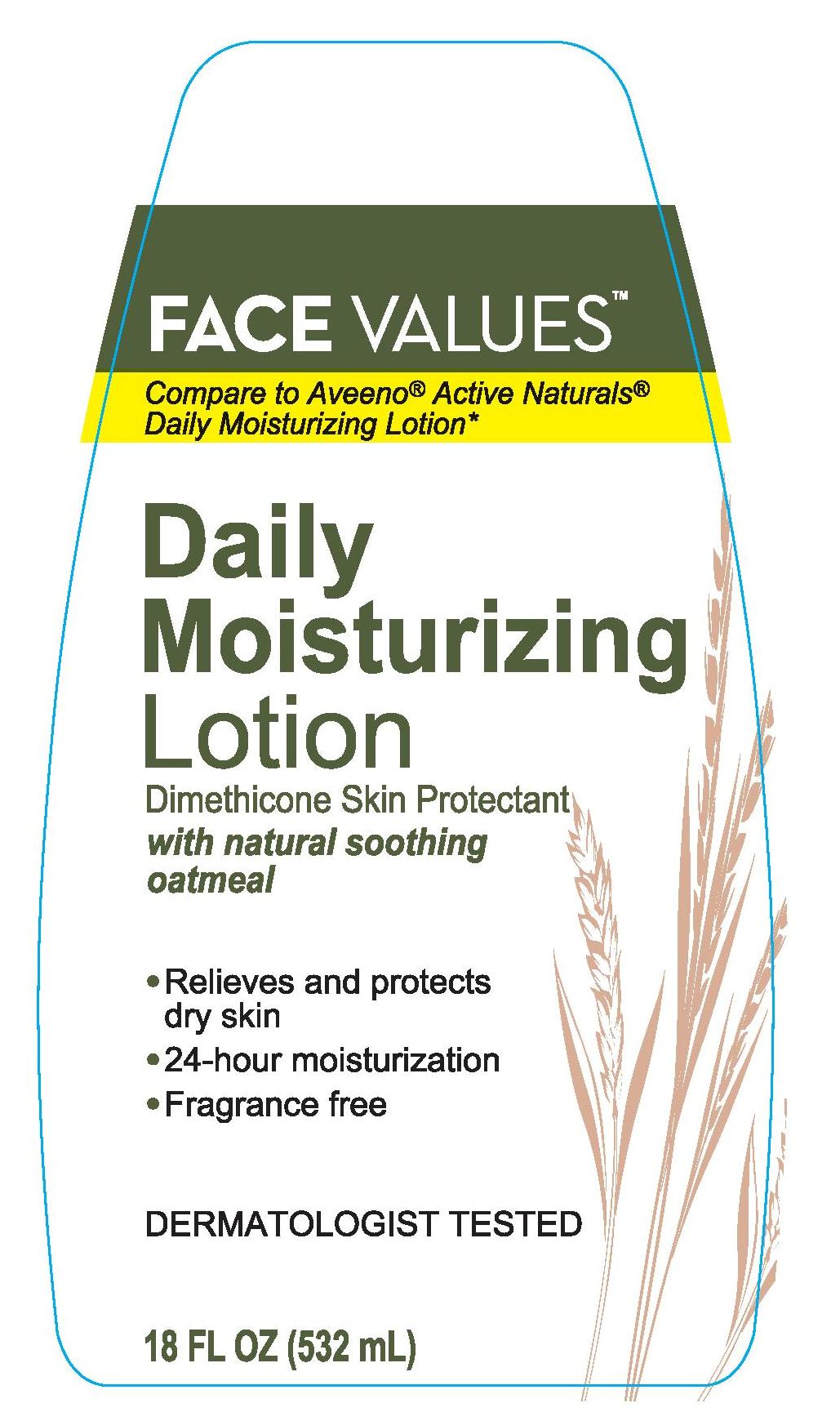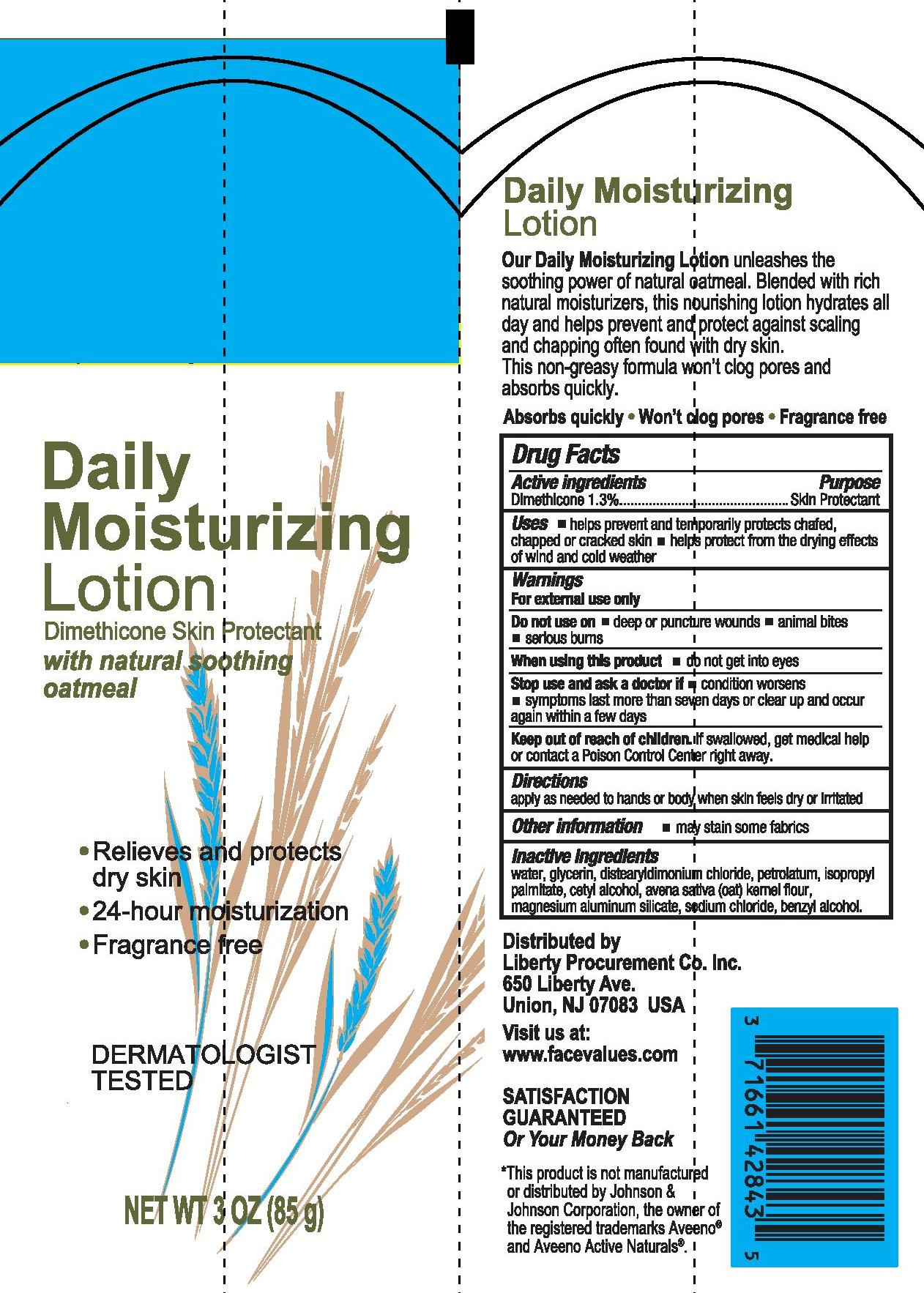 DRUG LABEL: HARMON DAILY MOISTURZIER
NDC: 63940-074 | Form: LOTION
Manufacturer: HARMON STORES, INC.
Category: otc | Type: HUMAN OTC DRUG LABEL
Date: 20241021

ACTIVE INGREDIENTS: DIMETHICONE 13 mg/1 mL
INACTIVE INGREDIENTS: WATER; GLYCERIN; DISTEARYLDIMONIUM CHLORIDE; PETROLATUM; ISOPROPYL PALMITATE; CETYL ALCOHOL; OATMEAL; BENZYL ALCOHOL; MAGNESIUM ALUMINUM SILICATE; SODIUM CHLORIDE

HARMON DAILY MOISTURIZING LOTION WITH NATURAL SOOTHING OATMEAL

Active ingredients

Dimethicone 1.3%

Purpose

Skin Protectant

Uses

- helps prevent and temporarily protects dry, chafed, cracked, and windburned skin.

Warnings

For external use only

Do not use

- on deep or puncture wounds, infections, or lacerations, Consult a doctor.

When using this product

- Keep out of eyes and eyelids. May stain or damage some fabrics, materials or surfaces.

Stop use and ask a doctor if

- condition worsens or does not improve within seven days.

Keep out of reach of children.

- If swallowed, get medical help or contact a Poison Control Center right away.

Directions

- Apply as needed to hands or body when skin feels dry or irritated.

Inactive ingredients

water, glycerin, distearyldimonium chloride, petrolatum, isopropyl palmitate, cetyl alcohol, avena sativa (oat) kernel flour, magnesium aluminum silicate, sodium chloride, benzyl alcohol

PACKAGE LABEL

HARMON DAILY MOISTURIZING LOTION WITH NATURAL SOOTHING OATMEAL

3 OZ (85g)

NDC 63940-072-03

HARMON DAILY MOISTURIZING LOTION WITH NATURAL SOOTHING OATMEAL

18 FL OZ (532mL)

NDC 63940-072-43